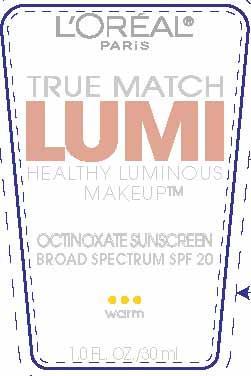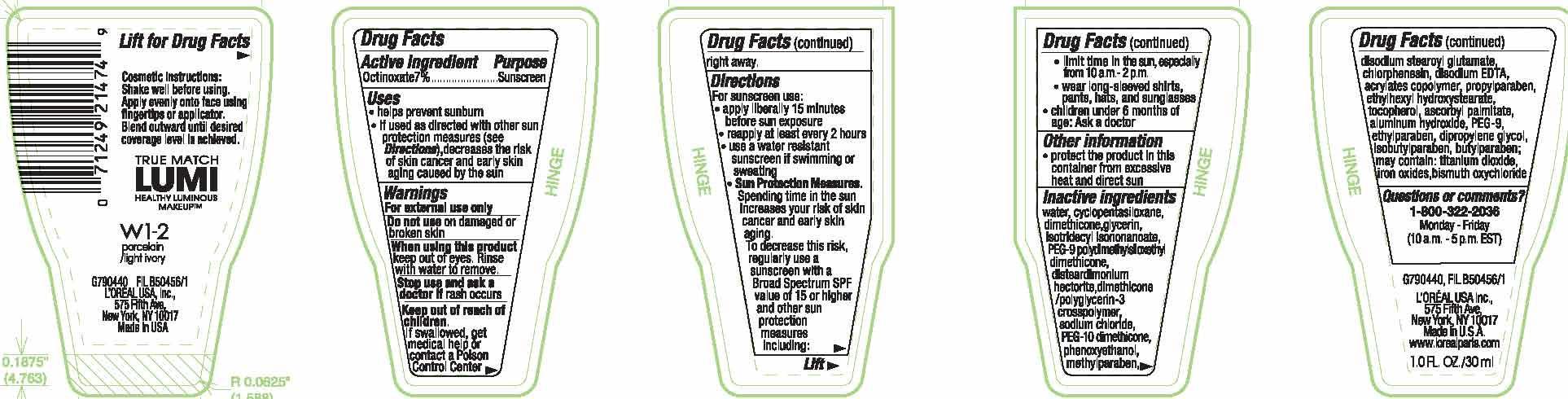 DRUG LABEL: LOreal Paris True Match Lumi Healthy Luminous Makeup Broad Spectrum SPF 20
NDC: 49967-475 | Form: LIQUID
Manufacturer: L'Oreal USA Products Inc
Category: otc | Type: HUMAN OTC DRUG LABEL
Date: 20231229

ACTIVE INGREDIENTS: OCTINOXATE 70 mg/1 mL
INACTIVE INGREDIENTS: WATER; DIMETHICONE; GLYCERIN

Drug Facts

Active ingredient

Octinoxate 7%

Purpose

Sunscreen

Uses

- helps prevent sunburn

- if used as directed with other sun protection measures (see Directions), decreases the risk of skin cancer and early skin aging caused by the sun

Warnings

For external use only

Do not use

on damaged or broken skin

When using this product

keep out of eyes. Rinse with water to remove.

Stop use and ask a doctor if

rash occurs

Keep out of reach of children.

If swallowed, get medical help or contact a Poison Control Center right away.

Directions

For sunscreen use:

● apply liberally 15 minutes before sun exposure

● reapply at least every 2 hours

● use a water resistant sunscreen if swimming or sweating

● Sun Protection Measures. Spending time in the sun increases your risk of skin cancer and early skin aging. To decrease this risk, regularly use a sunscreen with a Broad Spectrum SPF value of 15 or higher and other sun protection measures including:

● limit time in the sun, especially from 10 a.m. – 2 p.m.

● wear long-sleeved shirts, pants, hats, and sunglasses

● children under 6 months of age: Ask a doctor

Other information

protect the product in this container from excessive heat and direct sun

Inactive ingredients

water, cyclopentasiloxane, dimethicone, glycerin, isotridecyl isononanoate, PEG-9 poly dimethylsiloxethyl dimethicone, disteardimonium hectorite, dimethicone/polyglycerin-3 crosspolymer, sodium chloride, PEG-10 dimethicone, phenoxyethanol, methylparaben, disodium stearoyl glutamate, chlorphenesin, disodium EDTA, acrylates copolymer, propylparaben, ethylhexyl hydroxystearate, tocopherol, ascorbyl palmitate, aluminum hydroxide, PEG-9, ethylparaben, dipropylene glycol, isobutylparaben, butylparaben; may contain: titanium dioxide, iron oxides, bismuth oxychloride

Questions or comments?

1-800-322-2036

Monday - Friday

(10 a.m. - 5 p.m. EST)